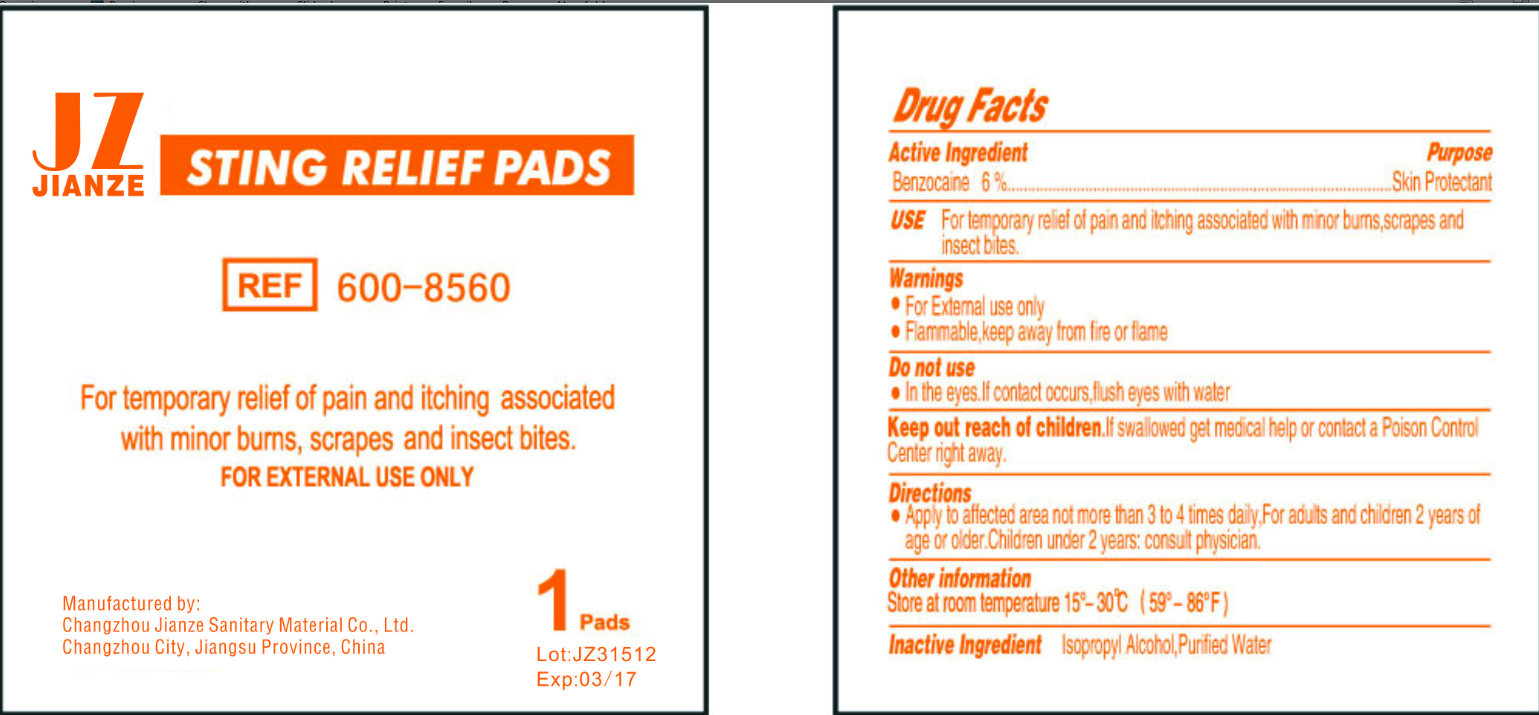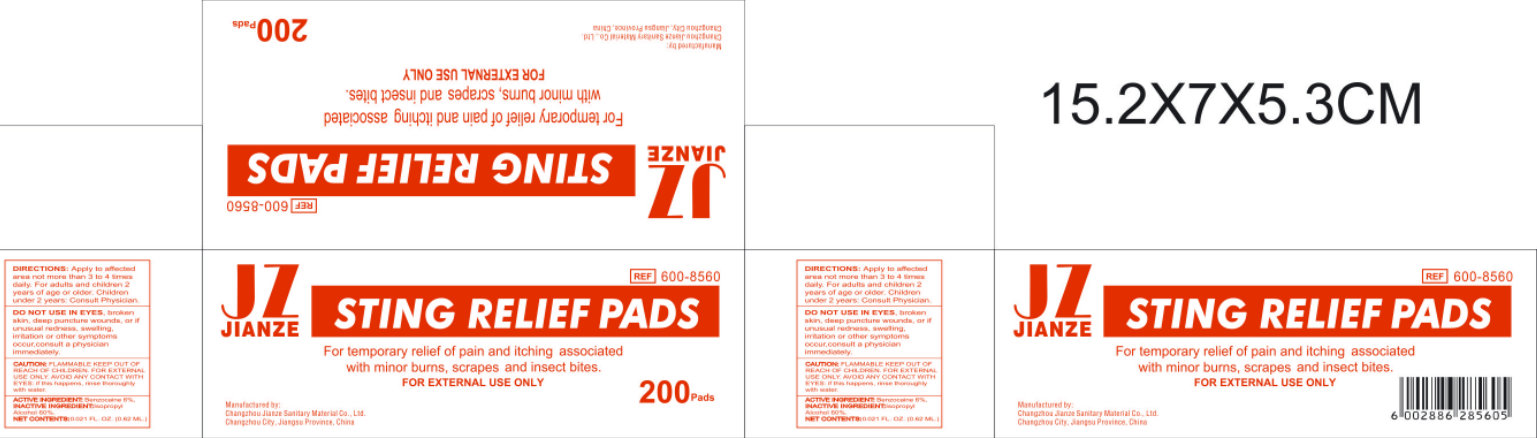 DRUG LABEL: JIANZE STING RELIEF PADS
NDC: 50666-008 | Form: LIQUID
Manufacturer: Changzhou Jianze Sanitary Material Co., Ltd.
Category: otc | Type: HUMAN OTC DRUG LABEL
Date: 20120620

ACTIVE INGREDIENTS: BENZOCAINE 6 g/100 g
INACTIVE INGREDIENTS: ISOPROPYL ALCOHOL; WATER

JIANZE STING RELIEF PADS

ACTIVE INGREDIENT

Benzocaine 6%

PURPOSE

Skin Protectant

USE:

For temporary relief of pain and itching associated with minor burns, scrapes and insect bites.

WARNINGS:

- For External Use Only
- Flammable, keep away from flame.

DO NOT USE

- In the eyes. If contact occurs, flush eyes with water.

KEEP OUT OF REACH OF CHILDREN.

In swallowed get medical help or contact a Poison Control Center right away.

DIRECTIONS

- Apply to affected area not more than 3 to 4 times daily, For adults and children 2 years of age or older. Children under 2 years: consult a physician.

OTHER INFORMATION

Store at room temperature 15 degrees - 30 degrees C (59 degrees - 86 degrees F)

INACTIVE INGREDIENTS:

Isopropyl Alcohol, Purified Water